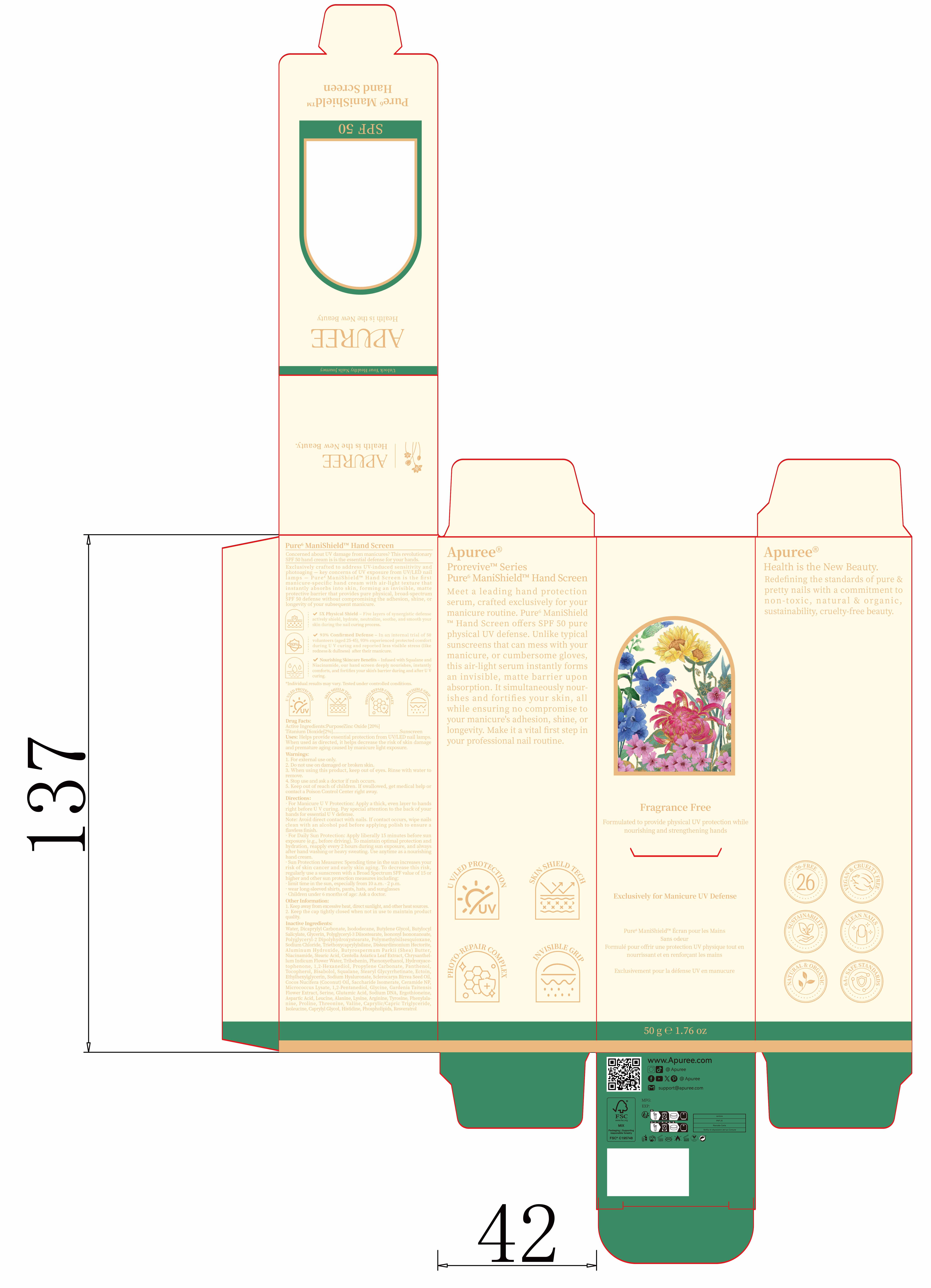 DRUG LABEL: Pure6 ManiShield Hand Screen
NDC: 85966-002 | Form: LIQUID
Manufacturer: GUANGZHOU SAWEILAN IMPORT & EXPORT TRADING CO., LTD
Category: otc | Type: HUMAN OTC DRUG LABEL
Date: 20250902

ACTIVE INGREDIENTS: ZINC OXIDE 10 g/50 g; TITANIUM DIOXIDE 2.5 g/50 g
INACTIVE INGREDIENTS: TRIETHOXYCAPRYLYLSILANE; SODIUM CHLORIDE; PHENYLALANINE; ALUMINUM HYDROXIDE; NIACINAMIDE; SQUALANE; THREONINE; CENTELLA ASIATICA WHOLE; DICAPRYLYL CARBONATE; LYSINE; ETHYLHEXYLGLYCERIN; SODIUM HYALURONATE; VALINE; PHOSPHOLIPID PHOSPHATASE 1; POLYMETHYLSILSESQUIOXANE/TRIMETHYLSILOXYSILICATE; BISABOLOL; STEARIC ACID; PENTYLENE GLYCOL; BUTYROSPERMUM PARKII (SHEA) BUTTER; PHENOXYETHANOL; 1,2-HEXANEDIOL; POLYGLYCERYL-3 DIISOSTEARATE; MICROCOCCUS LUTEUS; WATER; STEARYL GLYCYRRHETINATE; ARGININE; CAPRYLIC/CAPRIC TRIGLYCERIDE; ECTOIN; HYDROXYACETOPHENONE; GARDENIA TAITENSIS FLOWER; HISTIDINE; COCOS NUCIFERA (COCONUT) OIL; LEUCINE; CERAMIDE NP; SERINE; SODIUM; PROLINE; GLYCINE; GLUTAMIC ACID; RESVERATROL; BUTYLENE GLYCOL; GLYCERIN; POLYGLYCERYL-2 DIPOLYHYDROXYSTEARATE; TRIBEHENIN; CAPRYLYL GLYCOL; PROPYLENE CARBONATE; BUTYLOCTYL SALICYLATE; CHRYSANTHELLUM INDICUM FLOWER OIL; POLYMETHYLSILSESQUIOXANE (4.5 MICRONS); TYROSINE; SCLEROCARYA BIRREA SEED OIL; SACCHARIDE ISOMERATE; ASPARTIC ACID; ALANINE; ISONONYL ISONONANOATE; ERGOTHIONEINE; PANTHENOL; TOCOPHEROL; ISOLEUCINE

85966-002 Pure6 ManiShield Hand Screen

ACTIVE INGREDIENT

ZINC OXIDE
TITANIUM DIOXIDE

PURPOSE

Sunscreen

INDICATIONS AND USAGE

Uses: Helps provide essential protection from UV LED nail lamps.When used as directed, it helps decrease the risk of skin damageandpremature aging caused by manicure light exposure.

WARNINGS

1. For external use only

Do not use on damaged or broken skin.

When using this product, keep out of eyes, Rinse with water toremove.

Stop use and ask a doctor if rash occurs.

Keep out of reach of children, If swallowed, get medical help orcontact a Poison Control Center right away.

DOSAGE AND ADMINISTRATION

. For Manicure UV Protection: Apply a thick, even layer to hands right before U V curing. Pay special attention to the back of yourhands for essentialUVdefense.
Note: Avoid direct contact with nails. If contact occurs, wipe nailsclean with an alcohol pad before applying polish to ensure a fawless finish.
. For Daily Sun Protection: Apply liberally 15 minutes before sunexposure (e.g., before driving). To maintain optimal protection andhydration, reapply every 2 hours during sun exposure, and alwaysafter hand washing or heavy sweating. Use anytime as a nourishinghand cream.
.Sun Protection Measures: Spending time in the sun increases yourrisk of skin cancer and early skin aging. To decrease this risk,regularlyuse a sunscreen with a Broad Spectrum SPF value of 15 orhigher and other sun protection measures including:
.limit time in the sun, especially from 10 a.m.-2 p.m.
.wear long-sleeved shirts, pants, hats, and sunglasses
.Childrenunder 6 months of age: Ask a doctor.

INACTIVE INGREDIENT

WATER
DICAPRYLYL CARBONATE
BUTYLENE GLYCOL
BUTYLOCTYL SALICYLATE
GLYCERIN
ISONONYL ISONONANOATE
POLYGLYCERYL-3 DIISOSTEARATE
POLYGLYCERYL-2 DIPOLYHYDROXYSTEARATE
POLYMETHYLSILSESQUIOXANE
SODIUM CHLORIDE
TRIETHOXYCAPRYLYLSILANE
DISTEARDIMONIUM HECTORITE
ALUMINUM HYDROXIDE
STEARIC ACID
BUTYROSPERMUM PARKII (SHEA) BUTTER
NIACINAMIDE
CENTELLA ASIATICA LEAF EXTRACT
CHRYSANTHELLUM INDICUM FLOWER WATER
TRIBEHENIN
PHENOXYETHANOL
HYDROXYACETOPHENONE
1,2-HEXANEDIOL
PROPYLENE CARBONATE
PANTHENOL
TOCOPHEROL
BISABOLOL
STEARYL GLYCYRRHETINATE
SQUALANE
ECTOIN
ETHYLHEXYLGLYCERIN
SODIUM HYALURONATE
SCLEROCARYA BIRREA SEED OIL
COCOS NUCIFERA (COCONUT) OIL
SACCHARIDE ISOMERATE
CERAMIDE NP
MICROCOCCUS LYSATE
PENTYLENE GLYCOL
GLYCINE
GARDENIA TAITENSIS FLOWER EXTRACT
SERINE
GLUTAMIC ACID
SODIUM DNA
ERGOTHIONEINE
ASPARTIC ACID
LEUCINE
ALANINE
LYSINE
ARGININE
TYROSINE
PHENYLALANINE
PROLINE
THREONINE
VALINE
CAPRYLIC/CAPRIC TRIGLYCERIDE
ISOLEUCINE
CAPRYLYL GLYCOL
HISTIDINE
PHOSPHOLIPIDS
RESVERATROL